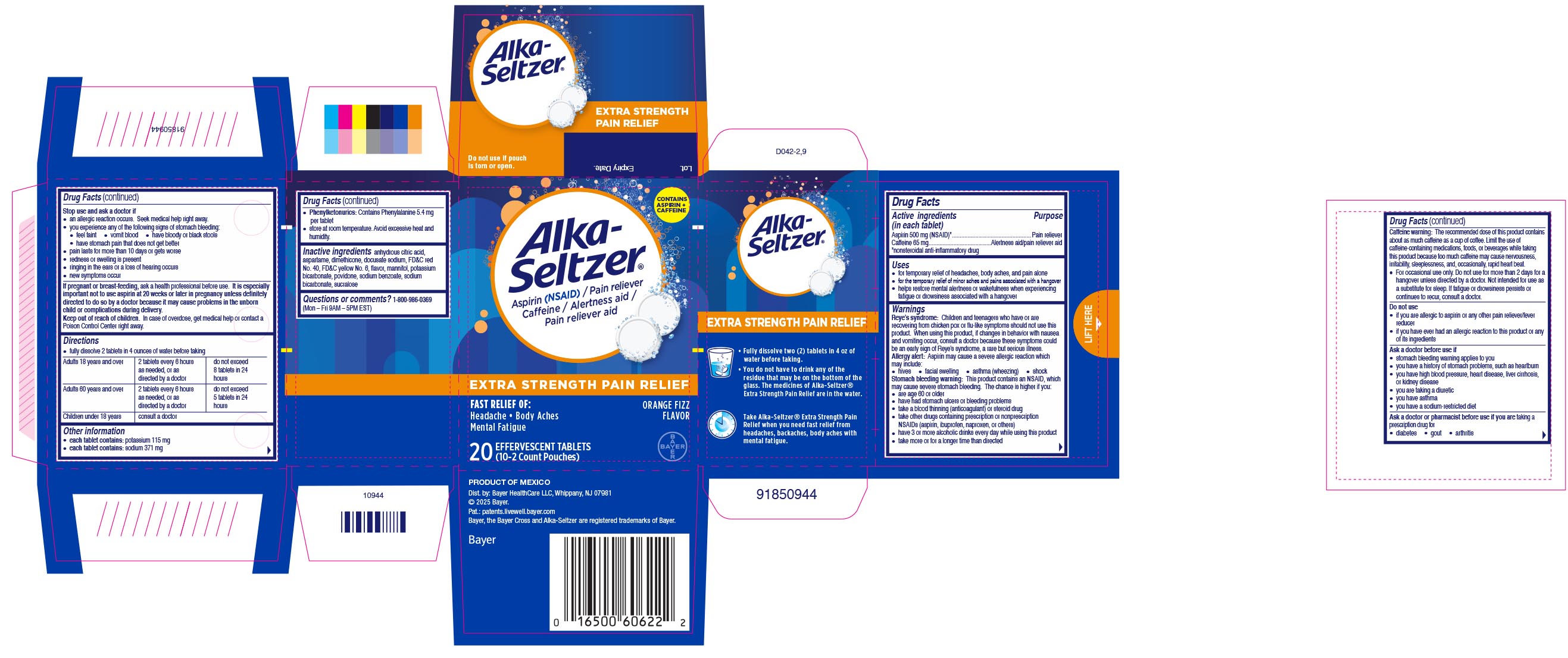 DRUG LABEL: Alka-Seltzer Extra Strength Pain Relief
NDC: 0280-8260 | Form: TABLET, EFFERVESCENT
Manufacturer: Bayer HealthCare LLC.
Category: otc | Type: HUMAN OTC DRUG LABEL
Date: 20260205

ACTIVE INGREDIENTS: CAFFEINE 65 mg/1 1; ASPIRIN 500 mg/1 1
INACTIVE INGREDIENTS: SODIUM BICARBONATE; SUCRALOSE; SODIUM BENZOATE; FD&C YELLOW NO. 6; ASPARTAME; ANHYDROUS CITRIC ACID; DOCUSATE SODIUM; DIMETHICONE 100; FD&C RED NO. 40; POTASSIUM BICARBONATE; CALCIUM SILICATE; POVIDONE; MANNITOL

Alka-Seltzer Extra Strength Pain Relief UI1614788

Drug Facts

Active Ingredients (in each tablet)
Aspirin 500 mg (NSAID)*
Caffeine 65 mg
*nonsteroidal anti-inflammatory drug

PURPOSE

Pain reliever
Alertness aid/pain reliever aid

Uses

- for temporary relief of headaches, body aches, and pain alone
- for the temporary relief of minor aches and pains associated with a hangover
- helps restore mental alertness or wakefulness when experiencing fatigue or drowsiness associated with a hangover

Warnings

Reye’s syndrome: Children and teenagers who have or are
recovering from chicken pox or flu-like symptoms should not use this product. When using this
product, if changes in behavior with nausea and vomiting occur, consult a doctor because these
symptoms could be an early sign of Reye’s syndrome, a rare but serious illness.
Allergy alert: Aspirin may cause a severe allergic reaction which may include:
● hives ● facial swelling ● asthma (wheezing) ● shock
Stomach bleeding warning: This product contains an NSAID, which may cause severe stomach bleeding.
The chance is higher if you:
● are age 60 or older
● have had stomach ulcers or bleeding problems
● take a blood thinning (anticoagulant) or steroid drug
● take other drugs containing prescription or nonprescription NSAIDs (aspirin, ibuprofen,
naproxen, or others)
● have 3 or more alcoholic drinks every day while using this product
● take more or for a longer time than directed
Caffeine warning: The recommended dose of this product contains about as much caffeine as a cup of
coffee. Limit the use of caffeine- containing medications, foods, or beverages while taking this
product because too much caffeine may cause nervousness, irritability, sleeplessness, and,
occasionally, rapid heart beat.
● For occasional use only. Do not use for more than 2 days for a hangover unless directed by a
doctor. Not intended for use as a substitute for sleep. If fatigue or drowsiness persists or
continues to recur, consult a doctor.

Reye's syndrome

Children and teenagers who have or are recovering from chicken pox or flu-like symptoms should not use this product. When using this product, if changes in behavior with nausea and vomiting occur, consult a doctor because these symptoms could be an early sign of Reye's syndrome, a rare but serious illness.

Allergy alert

Aspirin may cause a severe allergic reaction which may include:
● hives ● facial swelling ● asthma (wheezing) ● shock

Stomach bleeding warning

This product contains an NSAID, which may cause severe stomach bleeding. The chance is higher if you:

- are age 60 or older
- have had stomach ulcers or bleeding problems
- take a blood thinning (anticoagulant) or steroid drug
- take other drugs containing prescription or nonprescription NSAIDs (aspirin, ibuprofen, naproxen, or others)
- have 3 or more alcoholic drinks every day while using this product
- take more or for a longer time than directed

Caffeine warning

The recommended dose of this product contains about as much caffeine as a cup of
coffee. Limit the use of caffeine- containing medications, foods, or beverages while taking this
product because too much caffeine may cause nervousness, irritability, sleeplessness, and,
occasionally, rapid heart beat.
● For occasional use only. Do not use for more than 2 days for a hangover unless directed by a
doctor. Not intended for use as a substitute for sleep. If fatigue or drowsiness persists or
continues to recur, consult a doctor.

Do not use

- if you are allergic to aspirin or any other pain reliever/fever reducer
- if you have ever had an allergic reaction to this product or any of its ingredients

Ask a doctor before use if

- stomach bleeding warning applies to you
- you have a history of stomach problems, such as heartburn
- you have high blood pressure, heart disease, liver cirrhosis, or kidney disease
- you are taking a diuretic
- you have asthma
- you have a sodium-restricted diet

Ask a doctor or pharmacist before use if you are

taking a prescription drug for
● diabetes ● gout ● arthritis

Stop use and ask a doctor if

- an allergic reaction occurs. Seek medical help right away.
- you experience any of the following signs of stomach bleeding:
  - feel faint
  - vomit blood
  - have bloody or black stools
  - have stomach pain that does not get better
- pain lasts for more than 10 days or gets worse
- redness or swelling is present
- ringing in the ears or a loss of hearing occurs
- new symptoms occur

PREGNANCY OR BREAST FEEDING

If pregnant or breast-feeding, ask a health professional before use. It is especially important
not to use aspirin at 20 weeks or later in pregnancy unless definitely directed to do so by a
doctor because it may cause problems in the unborn child or complications during delivery.

Keep out of reach of children. In case of overdose, get medical help or contact a Poison Control Center right away.

Directions

● fully dissolve 2 tablets in 4 ounces of water before taking

Adults 18 years and over | 2 tablets every 6 hours as needed, or as directed by a doctor | do not exceed 8 tablets in 24 hours
Adults 60 years and over | 2 tablets every 6 hours as needed, or as directed by a doctor | do not exceed 5 tablets in 24 hours
Children under 18 years | consult a doctor

Other information

● each tablet contains: potassium 115 mg
● each tablet contains: sodium 371 mg
● Phenylketonurics: Contains Phenylalanine 5.4 mg per tablet
● store at room temperature. Avoid excessive heat and humidity.

Inactive ingredients

anhydrous citric acid, aspartame, dimethicone, docusate sodium, FD&C red No. 40, FD&C yellow No. 6, flavor, mannitol, potassium
bicarbonate, povidone, sodium benzoate, sodium bicarbonate, sucralose

Questions or comments?

1-800-986-0369 (Mon – Fri 9AM – 5PM EST)